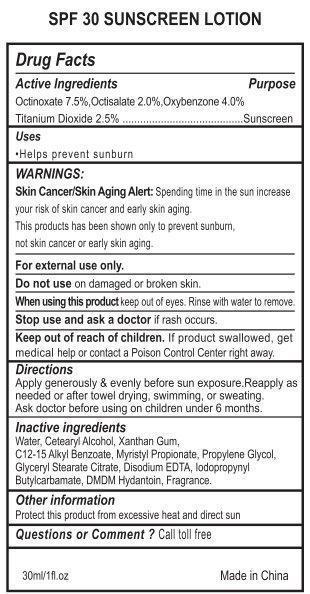 DRUG LABEL: Sunscreen SPF 30
NDC: 31190-210 | Form: LOTION
Manufacturer: Shanghai Kejing Cleaning Products Co., Ltd
Category: otc | Type: HUMAN OTC DRUG LABEL
Date: 20140513

ACTIVE INGREDIENTS: OCTINOXATE 75 mg/1 mL; OCTISALATE 20 mg/1 mL; OXYBENZONE 40 mg/1 mL; TITANIUM DIOXIDE 2.5 mg/1 mL
INACTIVE INGREDIENTS: WATER; CETOSTEARYL ALCOHOL; XANTHAN GUM; ALKYL (C12-15) BENZOATE; MYRISTYL PROPIONATE; PROPYLENE GLYCOL; GLYCERYL STEARATE CITRATE; EDETATE DISODIUM; IODOPROPYNYL BUTYLCARBAMATE; DMDM HYDANTOIN

SPF 30 Sunscreen Lotion

Active Ingredients

Octinoxate 7.5%, Octisalate 2.0%, Oxybenzone 4.0%, Titanium Dioxide 2.5%

Purpose

Sunscreen

Uses

Helps prevent sunburn

Warnings

Skin Cancer/Skin Aging Alert: Spending time in the sun increase your risk of skin cancer and early skin aging. This products has been shown only to prevent sunburn, not skin cancer or early skin aging

For External use only.

Do not use

on damaged or broken skin.

When using this product

Keep out of eyes. Rinse with water to remove.

Stop use and ask a doctor

f rash occurs.

Keep out of Reach of Children

If product swallowed, get medical help or contact a Poison Control Center right away.

Directions

Apply generously & evenly before sun exposure.Reapply as needed or after towel drying, swimming, or sweating.

Ask doctor before using on children under 6 months.

Inactive Ingredients

Water, Cetearyl Alcohol, Xanthan Gum, C12-15 Alkyl Benzoate, Myristyl Propionate, Propylene Glycol, Glyceryl Stearate Citrate, Disodium EDTA, Iodopropynyl Butylcarbamate, DMDM Hydantoin, Fragrance.

Other information

Protect this product from excessive heat and direct sun

Questions or Comment ?

Call toll free